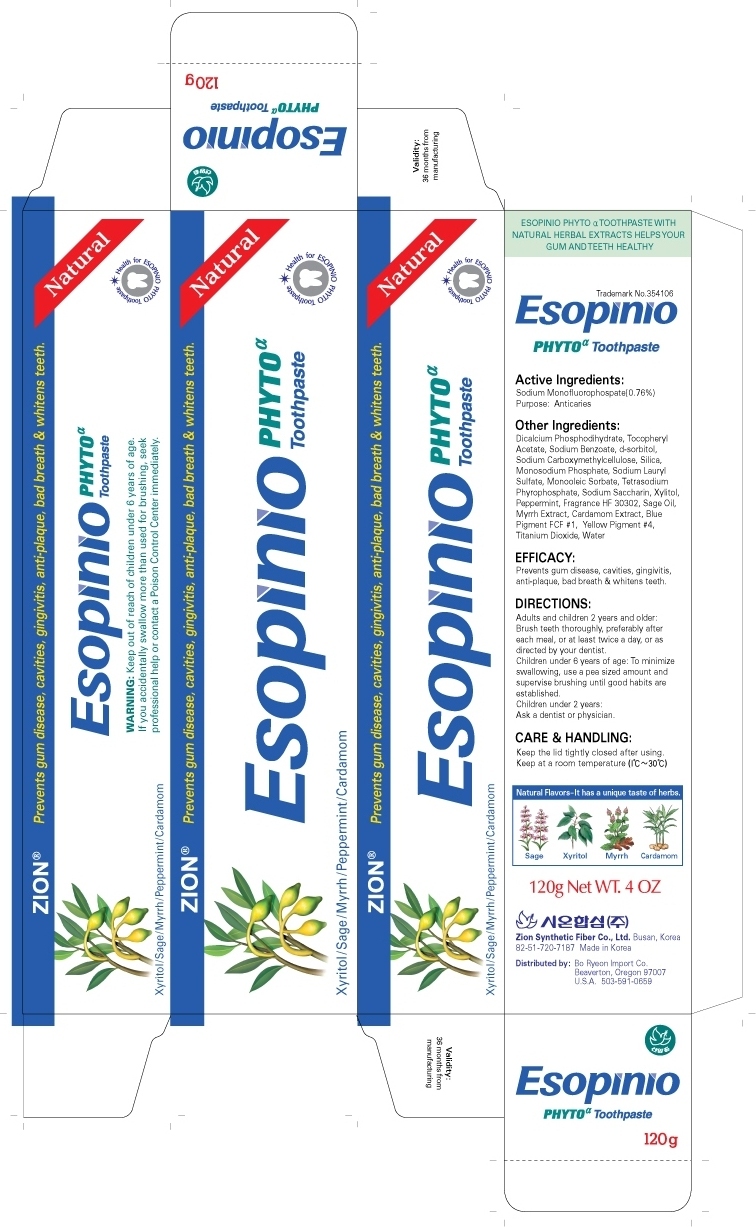 DRUG LABEL: Escopinio PHYTO alpha Toothpaste
NDC: 44781-447 | Form: PASTE
Manufacturer: Zion Synthetic Fiber Corporation Limited
Category: otc | Type: HUMAN OTC DRUG LABEL
Date: 20100121

ACTIVE INGREDIENTS: SODIUM MONOFLUOROPHOSPHATE 0.912 g/120 g

Active Ingredients: Sodium Monofluorophosphate

INACTIVE INGREDIENT

Other Ingredients:
Water, Dicalcium Phosphodihydrate, Tocopheryl Acetate, Sodium Benzoate, d-Sorbitol, Sodium Carboxymethylcellulose, Silica, Monosodium Phosphate, Sodium Lauryl Sulfate, Monooleic Sorbate, Tetrasodium Pyrophosphate, Sodum Saccharin, Xylitol, Mentha (peppermint), Fragrance HF 30302, Sage Oil, Myrrh Extract, Cardamom Extract, Blue FCF #1, Yellow #4, Titanium Dioxide

Directions:
Adults and children 2 years and older:
Brush teeth thoroughly preferably after each meal or at least twice a day or as directed by your dentist.
Children under 6 years of age:
To minimize swallowing, use a pea sized amount and supervise brushing until good habits are established.
Children under 2 years: Ask a dentist or physician

Care and Handling:
Keep the lid tightly closed after using.
Keep at a room temperature